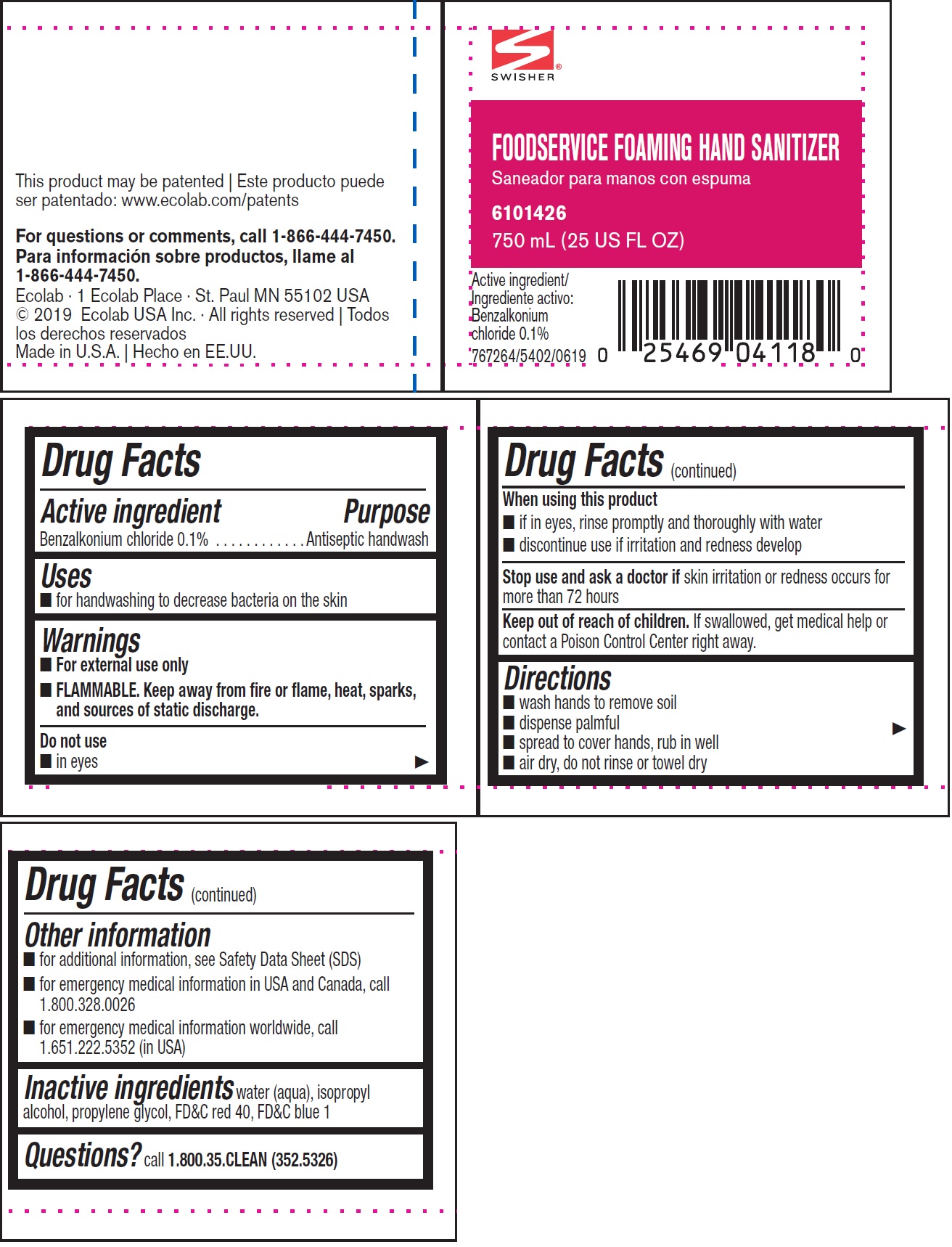 DRUG LABEL: Swisher
NDC: 47593-576 | Form: SOLUTION
Manufacturer: Ecolab Inc.
Category: otc | Type: HUMAN OTC DRUG LABEL
Date: 20240802

ACTIVE INGREDIENTS: BENZALKONIUM CHLORIDE 1 mg/1 mL
INACTIVE INGREDIENTS: WATER; ISOPROPYL ALCOHOL; PROPYLENE GLYCOL; FD&C RED NO. 40; FD&C BLUE NO. 1

Drug Facts

Active ingredient

Benzalkonium chloride 0.1%

Purpose

Antiseptic handwash

Uses

- for handwashing to decrease bacteria on the skin

Warnings

- For external use only
- FLAMMABLE. Keep away from fire or flame, heat, sparks, and sources of static discharge.

Do not use

- in eyes

When using this product

- if in eyes, rinse promptly and throughly with water
- discontinue use if irritation and redness develop

Stop use and ask doctor if skin irritation or redness persists for more than 72 hours

Keep out of reach of children. If swallowed, get medical help or contact a Poison Control Center right away.

Directions

- wash hands to remove soil
- dispense palmful
- spread to cover hands, rub in well
- air dry, do not rinse or towel dry

Other information

- for additional information, see Safety Data Sheet (SDS)
- for emergency medical information in USA and Canada, call 1.800.328.0026
- for emergency medical information worldwide, call 1.651.222.5352 (in USA)

INACTIVE INGREDIENT

Inactive ingredients water (aqua), isopropyl alcohol, propylene glycol, FD&C red 40, FD&C blue 1

Questions? call 1.800.35.CLEAN (352.5326)

Representative label and principal display panel

SWISHER

Foodservice Foaming Hand Sanitizer

Active Ingredient: Benzalkonium chloride 0.1%

6101426

750 mL (25 US FL OZ)

Active ingredient | Benzalkonium chloride 0.1%

767264/5402/0619

This product may be patented

www.ecolab.com/patents

For questions or comments, call 1-866-444-7450.

Ecolab · 1 Ecolab Place · St Paul MN 55102 USA

© 2019 Ecolab USA Inc. · All rights reserved

Made in U.S.A.